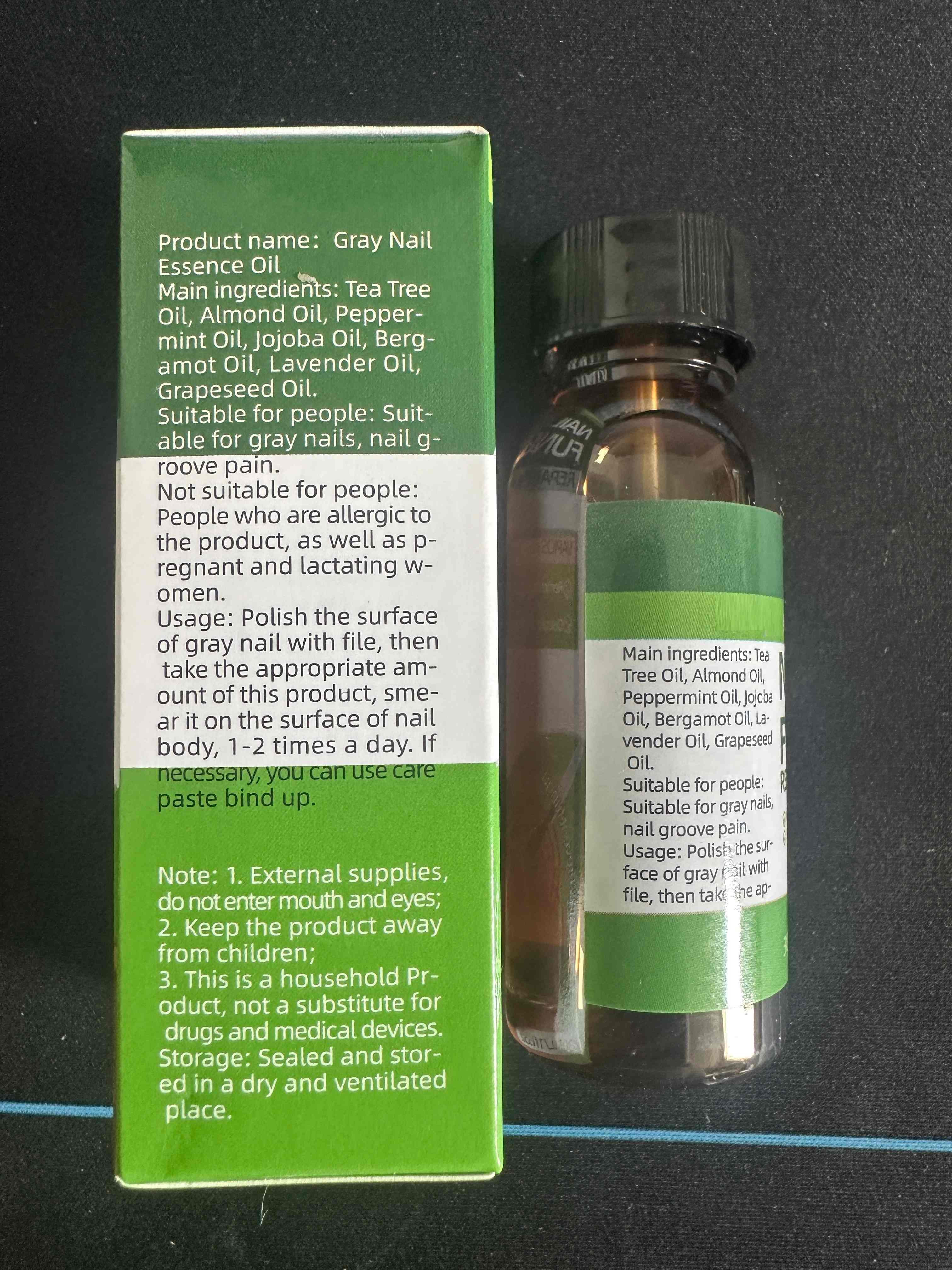 DRUG LABEL: Gray Nail Essence Oil
NDC: 85593-003 | Form: LIQUID
Manufacturer: Guangzhou ChuanMa International Trading Co.,Ltd.
Category: otc | Type: HUMAN OTC DRUG LABEL
Date: 20250715

ACTIVE INGREDIENTS: PEPPERMINT OIL 1 g/100 mL
INACTIVE INGREDIENTS: BERGAMOT OIL; JOJOBA OIL; ALMOND OIL; LAVENDER OIL; CHAMAEMELUM NOBILE FLOWER; GRAPE SEED OIL

ACTIVE INGREDIENT

Peppermint Oil 1%

INACTIVE INGREDIENT

Main ingredients: Tea TreeOil, Almond Oil, , jojoba Oil, Bergamot Oil, Lavender Oil,Grapeseed Oil

PURPOSE

VAPIOS HERBAL FORMULA
GRemoval of fungal infected nail
()Discoloration reduces

DOSAGE AND ADMINISTRATION

Usage: Polish the surfaceof gray nail with file, thentake the appropriate am-ount of this product, sme-ar it on the surface of nailbody,1-2 times a day. lfnecessary, you can use carepaste bind up.

STOP USE

Not suitable for people:People who are allergic tothe product, as well as pregnant and lactating w-omen.

WARNINGS

External supplies,do not enter mouth and eyes;2. Keep the product awayfrom children;3. This is a household Pr-oduct, not a substitute fordrugs and medical devices.Storage: Sealed and stor-ed in a dry and ventilatedplace.

Keep the product awayfrom children;

INDICATIONS AND USAGE

Usage: Polish the surfaceof gray nail with file, thentake the appropriate am-ount of this product, sme-ar it on the surface of nailbody,1-2 times a day. lfnecessary, you can use carepaste bind up.

OTHER SAFETY INFORMATION

This is a household Pr-oduct, not a substitute fordrugs and medical devices.Storage: Sealed and stor-ed in a dry and ventilatedplace.